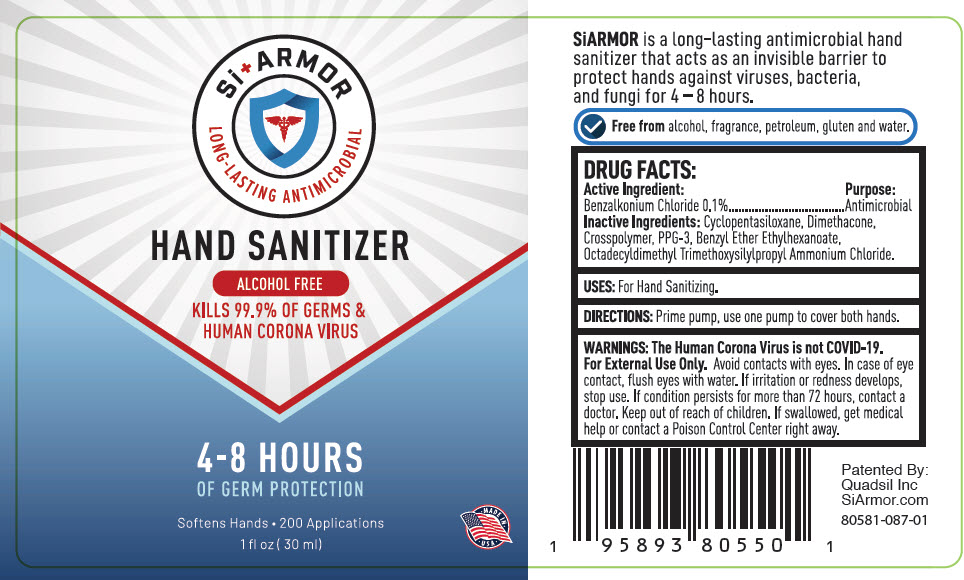 DRUG LABEL: HAND SANITIZER
NDC: 80581-087 | Form: GEL
Manufacturer: QuadSil Inc
Category: otc | Type: HUMAN OTC DRUG LABEL
Date: 20240312

ACTIVE INGREDIENTS: BENZALKONIUM CHLORIDE 1 mg/1 mL
INACTIVE INGREDIENTS: CYCLOMETHICONE 5; DIMETHICONE; TRIPROPYLENE GLYCOL

HAND SANITIZER

DRUG FACTS:

Active Ingredient

Benzalkonium Chloride 0.1%

Purpose

Antimicrobial

Inactive Ingredients

Cyclopentasiloxane, Dimethacone, Crosspolymer, PPG-3, Benzyl Ether Ethylhexanoate, Octadecyldimethyl Trimethoxysilylpropyl Ammonium Chloride.

USES

For Hand Sanitizing.

DIRECTIONS

Prime pump, use one pump to cover both hands.

WARNINGS

The Human Corona Virus is not COVID-19. For External Use Only. Avoid contacts with eyes. In case of eye contact, flush eyes with water. If irritation or redness develops, stop use. If condition persists for more than 72 hours, contact a doctor.

Keep out of reach of children. If swallowed, get medical help or contact a Poison Control Center right away.

Distributed By: Thor Microbials

PRINCIPAL DISPLAY PANEL - 30 ml Bottle Label

Si + ARMOR
LONG-LASTING ANTIMICROBIAL

HAND SANITIZER

ALCOHOL FREE

KILLS 99.9% OF GERMS &
HUMAN CORONA VIRUS

4-8 HOURS
OF GERM PROTECTION

Softens Hands • 200 Applications
1 fl oz (30 ml)

• MADE IN •
• USA •